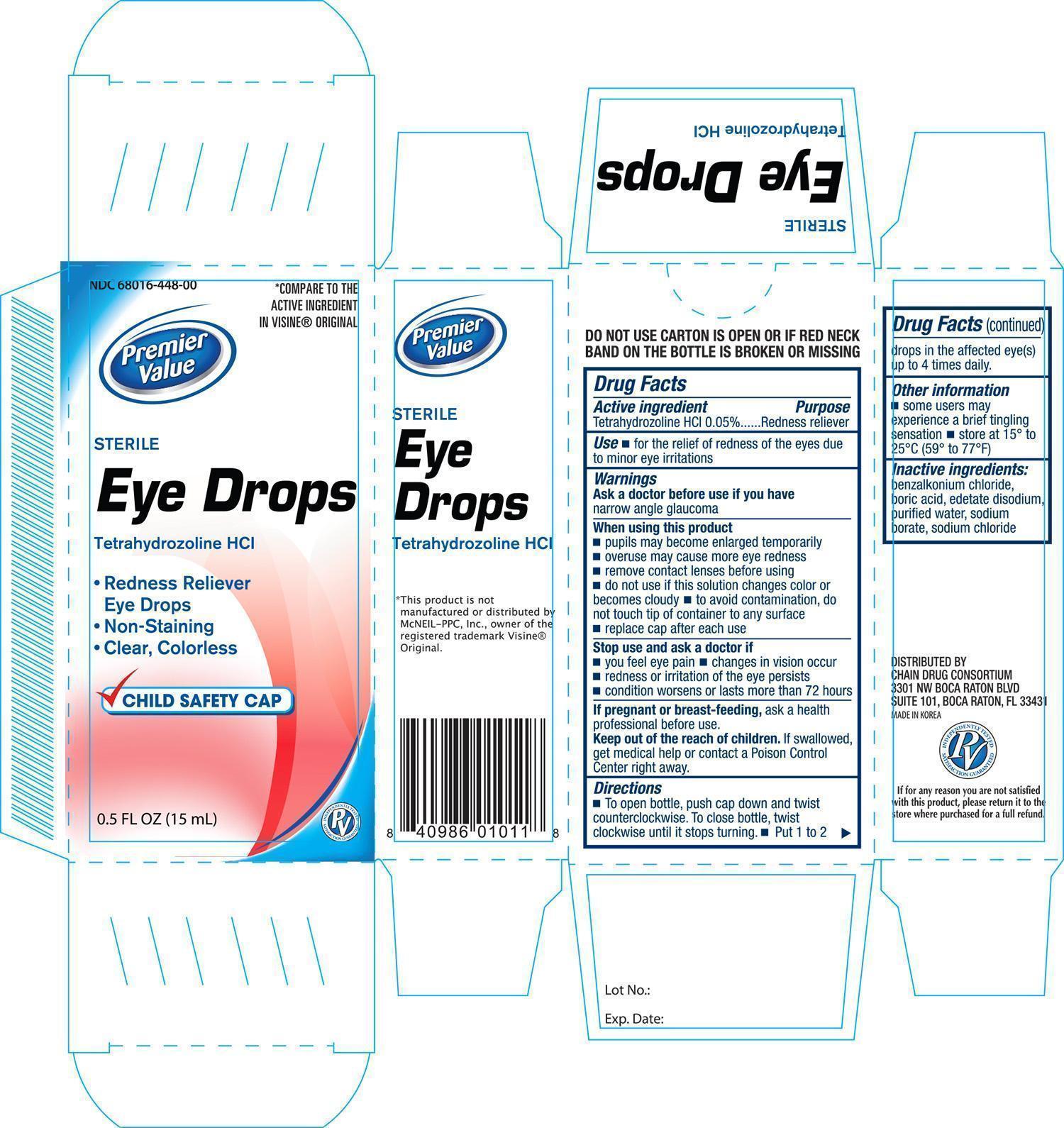 DRUG LABEL: Premier Value Original
NDC: 68016-448 | Form: SOLUTION/ DROPS
Manufacturer: Chain Drug Consortium, LLC
Category: otc | Type: HUMAN OTC DRUG LABEL
Date: 20150105

ACTIVE INGREDIENTS: TETRAHYDROZOLINE HYDROCHLORIDE 0.5 mg/1 mL
INACTIVE INGREDIENTS: BENZALKONIUM CHLORIDE; BORIC ACID; EDETATE DISODIUM; WATER; SODIUM BORATE; SODIUM CHLORIDE

Active Ingredient Purpose

Tetrahydrozoline HCl 0.05%........................... Redness Reliever

Use

- for the relief of redness of the eyes due to minor eye irritations

Warnings

Ask a doctor before use if you have narrow angle glaucoma

When using this product

- pupils may become enlarged temporarily
- overuse may cause more eye redness
- remove contact lenses before using
- do not use if this solution changes color or becomes cloudy
- to avoid contamination, do not touch tip of container to any surface
- replace cap after each use

Stop use and ask a doctor if

- you feel eye pain
- changes in vision occur
- redness or irritation of the eye persists
- condition worsens or lasts more than 72 hours

PREGNANCY OR BREAST FEEDING

If pregnant or breast-feeding, ask a health professional before use.

Keep out of the reach of children.

If swallowed, get medical help or contact a Poision Control Center right away.

Directions

- To open bottle, push cap down and twist counterclockwise. To close bottle, twist clockwise until it stops turning
- Put 1 to 2 drops in the affected eye(s) up to 4 times daily.

Other information

- some users may experience a brief tingling sensation
- store at 15° to 25°C (59° to 77°F)

Inactive ingredients:

benzalkonium chloride, boric acid, edetate disodium, purified water, sodium borate, sodium chloride

DOSAGE AND ADMINISTRATION

DISTRIBUTED BY:

CHAIN DRUG CONSORTIUM

3301 NW BOCA RATON BLVD

SUITE 101, BOCA RATON, FL 33431